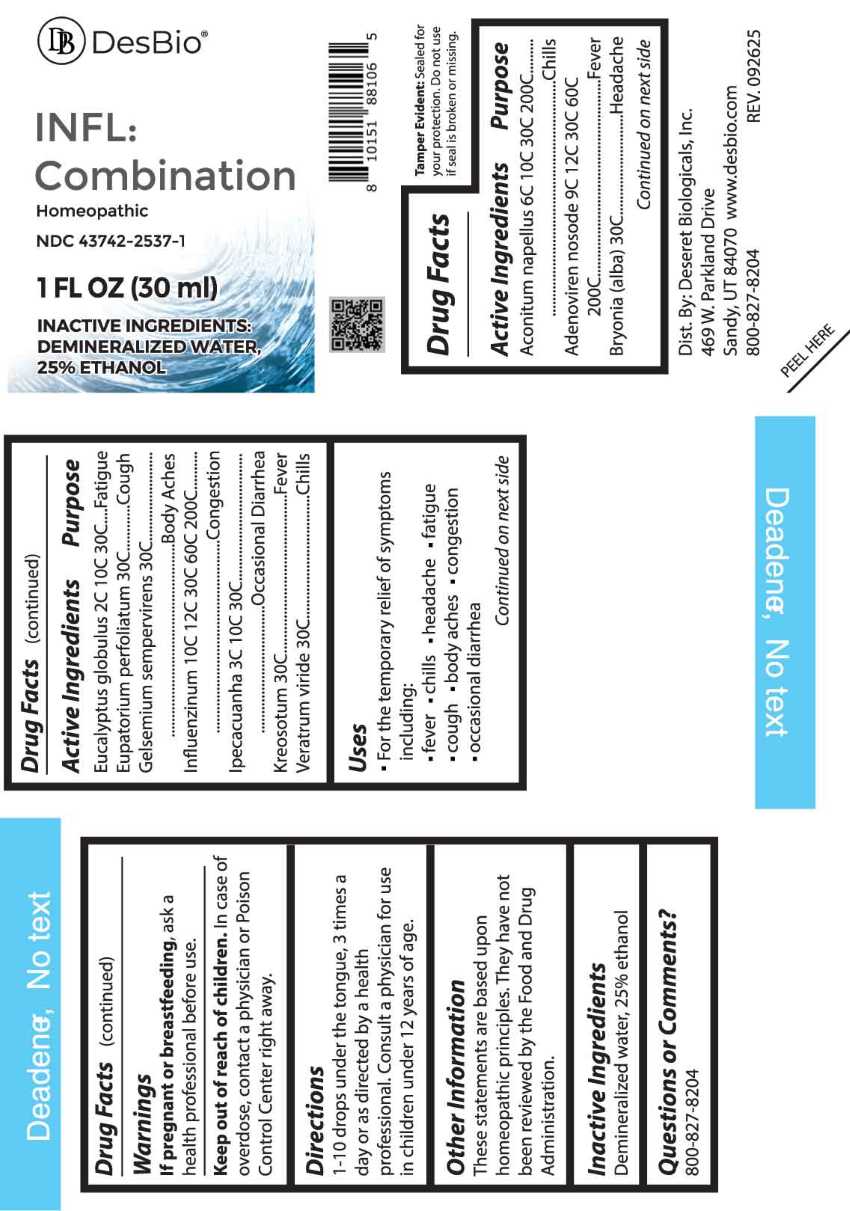 DRUG LABEL: INFL Combination
NDC: 43742-2537 | Form: LIQUID
Manufacturer: Deseret Biologicals, Inc.
Category: homeopathic | Type: HUMAN OTC DRUG LABEL
Date: 20260105

ACTIVE INGREDIENTS: ACONITUM NAPELLUS WHOLE 6 [hp_C]/1 mL; HUMAN ADENOVIRUS E SEROTYPE 4 STRAIN CL-68578 ANTIGEN 9 [hp_C]/1 mL; BRYONIA ALBA ROOT 30 [hp_C]/1 mL; EUCALYPTUS GLOBULUS LEAF 2 [hp_C]/1 mL; EUPATORIUM PERFOLIATUM FLOWERING TOP 30 [hp_C]/1 mL; GELSEMIUM SEMPERVIRENS ROOT 30 [hp_C]/1 mL; INFLUENZA A VIRUS A/VICTORIA/4897/2022 IVR-238 (H1N1) ANTIGEN (FORMALDEHYDE INACTIVATED) 10 [hp_C]/1 mL; INFLUENZA A VIRUS A/THAILAND/8/2022 IVR-237 (H3N2) ANTIGEN (FORMALDEHYDE INACTIVATED) 10 [hp_C]/1 mL; INFLUENZA B VIRUS B/AUSTRIA/1359417/2021 BVR-26 WHOLE 10 [hp_C]/1 mL; INFLUENZA B VIRUS B/PHUKET/3073/2013 BVR-1B WHOLE 10 [hp_C]/1 mL; IPECAC 3 [hp_C]/1 mL; WOOD CREOSOTE 30 [hp_C]/1 mL; VERATRUM VIRIDE ROOT 30 [hp_C]/1 mL
INACTIVE INGREDIENTS: WATER; ALCOHOL

DRUG FACTS:

ACTIVE INGREDIENTS:

Aconitum Napellus 6C, 10C, 30C, 200C, Adenoviren Nosode 9C, 12C, 30C, 60C, 200C, Bryonia (Alba) 30C, Eucalyptus Globulus 2C, 10C, 30C, Eupatorium Perfoliatum 30C, Gelsemium Sempervirens 30C, Influenzinum 10C, 12C, 30C, 60C, 200C, Ipecacuanha 3C, 10C, 30C, Kreosotum 30C, Veratrum Viride 30C.

PURPOSE:

Aconitum Napellus - Chills, Adenoviren Nosode - Fever, Bryonia (Alba) - Headache, Eucalyptus Globulus - Fatigue, Eupatorium Perfoliatum - Cough, Gelsemium Sempervirens – Body Aches, Influenzinum - Congestion, Ipecacuanha – Occasional Diarrhea, Kreosotum - Fever, Veratrum Viride - Chills

USES:

• For the temporary relief of symptoms including:

• fever • chills • headache • fatigue • cough • body aches • congestion • occasional diarrhea

These statements are based upon homeopathic principles. They have not been reviewed by the Food and Drug Administration.

WARNINGS:

If pregnant or breastfeeding, ask a health professional before use.

Keep out of reach of children. In case of overdose, contact a physician or Poison Control Center right away.

Tamper Evident: Sealed for your protection. Do not use if seal is broken or missing.

KEEP OUT OF REACH OF CHILDREN:

In case of overdose, contact physician or a Poison Control Center right away.

DIRECTIONS:

1-10 drops under the tongue, 3 times a day or as directed by a health professional. Consult a physician for use in children under 12 years of age.

INACTIVE INGREDIENTS:

Demineralized water, 25% ethanol

QUESTIONS:

Dist. By: Deseret Biologicals, Inc.
469 W. Parkland Drive
Sandy, UT 84070

www.desbio.com

800-827-8204

PACKAGE LABEL DISPLAY:

DesBio
INFL:Combination
Homeopathic
NDC 43742-2537-1
1 FL OZ (30 ml)